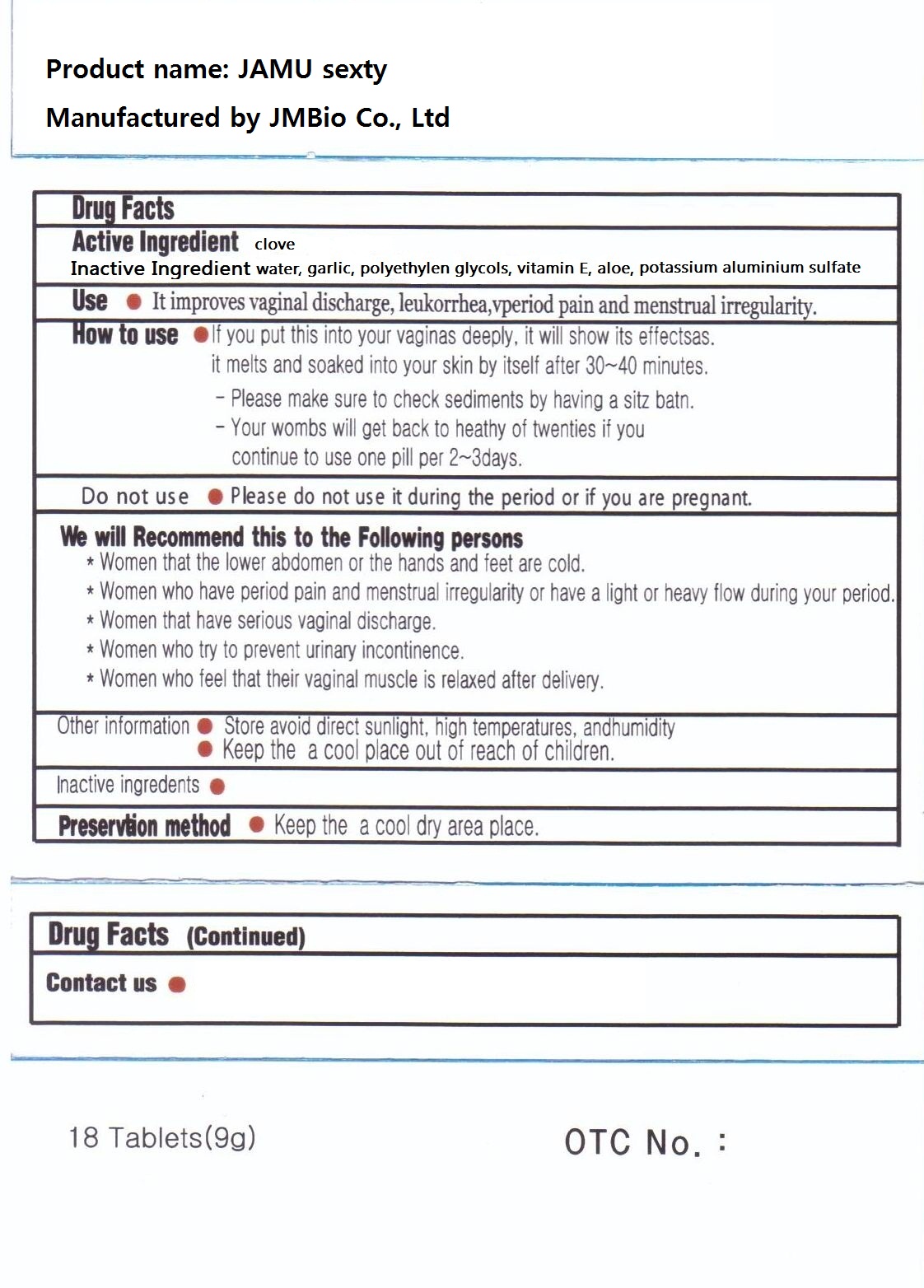 DRUG LABEL: JAMU Sexty
NDC: 42468-1001 | Form: TABLET
Manufacturer: JMBio Co., Ltd.
Category: otc | Type: HUMAN OTC DRUG LABEL
Date: 20120523

ACTIVE INGREDIENTS: CLOVE 18 mg/1 1
INACTIVE INGREDIENTS: ALUMINUM SULFATE; GARLIC; POLYETHYLENE GLYCOLS; ALPHA-TOCOPHEROL ACETATE; ALOE; WATER

Drug Facts

active ingredient: clove

inactive ingredient: water, garlic garlic, polyethylens glycols, vitamin E, aloe, aluminium sulfate, sepia esculenta, galla rhois

PURPOSE

improvement of vaginal discharge, leukorrhea, vperiod pain and menstrual irregularity

keep out of reach of the children

INDICATIONS AND USAGE

- if you put this into your vaginas deeply, it will show its effectsas
- it melts and soaked into your skin by itself after 30~40 minutes
- please make sure to check sediments by having a sitz batn
- your wombs will get back to healthy of twenties if you continue to use one pill per 2~3days

WARNINGS

- please do not use it during the period or if you are pregnant
- store avoid direct sunlight, high temperatures, and humidity
- keep in a cool and dry place

DOSAGE AND ADMINISTRATION

- women that the lower abdoment or the hands and feet are cold
- women who have period pain and menstrual irregularity or have a light or heavy flow during your period
- women that have serious vaginal discharge
- women who try to prevent urinary incontinence
- women who feel that their vaginal muscle is relaxed after delivery